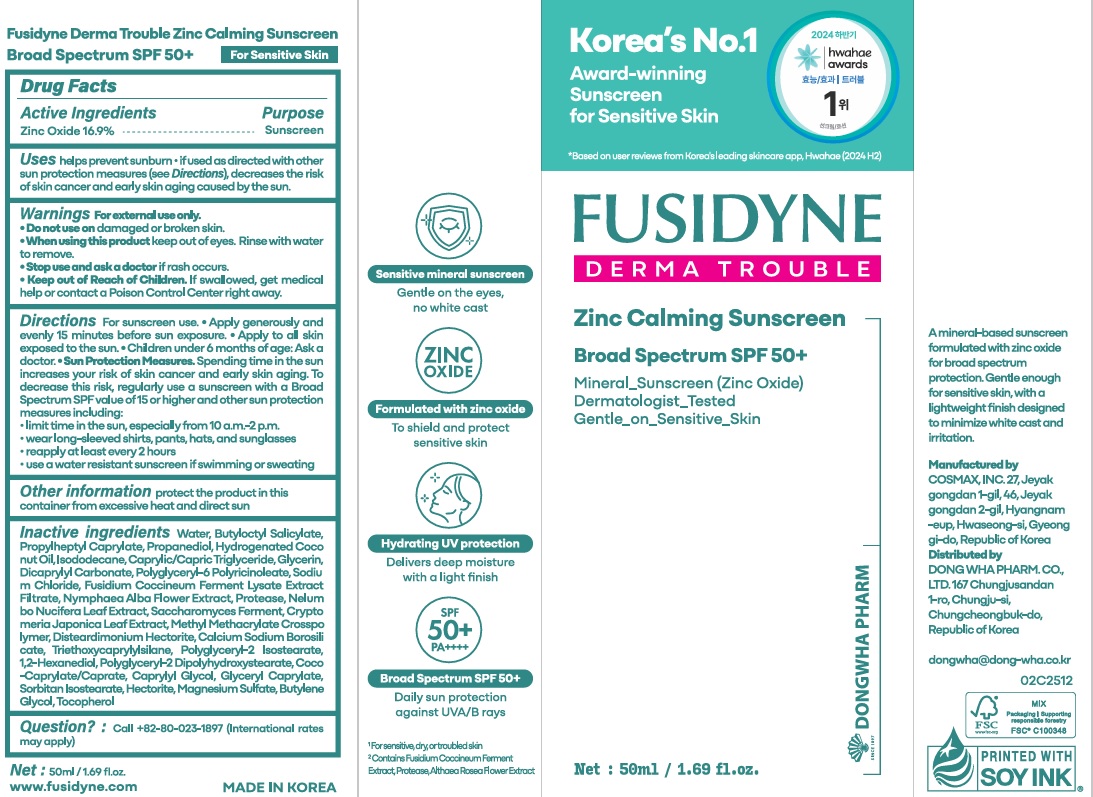 DRUG LABEL: FUSIDYNE DERMA TROUBLE Zinc Calming Sunscreen
NDC: 51352-999 | Form: LOTION
Manufacturer: DONG WHA PHARM. CO., LTD.
Category: otc | Type: HUMAN OTC DRUG LABEL
Date: 20251218

ACTIVE INGREDIENTS: ZINC OXIDE 8.463275 g/50 mL
INACTIVE INGREDIENTS: COCO-CAPRYLATE/CAPRATE; SORBITAN ISOSTEARATE; METHYL METHACRYLATE/GLYCOL DIMETHACRYLATE CROSSPOLYMER; POLYGLYCERYL-6 POLYRICINOLEATE; ISODODECANE; DICAPRYLYL CARBONATE; POLYGLYCERYL-2 ISOSTEARATE; NYMPHAEA ALBA FLOWER; TRIETHOXYCAPRYLYLSILANE; PROPANEDIOL; WATER; PROPYLHEPTYL CAPRYLATE; CAPRYLIC/CAPRIC TRIGLYCERIDE; CALCIUM SODIUM BOROSILICATE; POLYGLYCERYL-2 DIPOLYHYDROXYSTEARATE; GLYCERIN; GLYCERYL CAPRYLATE; 1,2-HEXANEDIOL; CRYPTOMERIA JAPONICA LEAF; NELUMBO NUCIFERA LEAF; MAGNESIUM SULFATE; HYDROGENATED COCONUT OIL; BUTYLOCTYL SALICYLATE; HECTORITE; TOCOPHEROL; SODIUM CHLORIDE; DISTEARDIMONIUM HECTORITE; CAPRYLYL GLYCOL; BUTYLENE GLYCOL

Active Ingredients-Zinc Oxide 16.9%

Purpose-Sunscreen

USES

helps prevent sunburn if used as directed with other sun protection measures, decreases the risk of skin cancer and early skin aging caused by the sun

Warning

Warnings
For external use only.

Do not use
• on damaged or broken skin

When using this product
• keep out of eyes. Rinse with water to remove.

Stop use and ask a doctor if
• rash occurs

Keep out of reach of children.
If swallowed, get medical help or contact a Poison Control Center right away.

Sun Protection Measures.
Spending time in the sun increases your risk of skin cancer and early skin aging.
To decrease this risk, regularly use a sunscreen with a Broad Spectrum SPF value of 15 or higher and other sun protection measures including:
• limit time in the sun, especially from 10 a.m.–2 p.m.
• wear long-sleeved shirts, pants, hats, and sunglasses

Directions

apply generously and evenly 15 minutes before sun exposure. apply to all skin exposed to the sun. reapply at least every 2 hours

use a water resistant sunscreen if swimming or sweating.children under 6 months of age: ask a doctor.

Other information

Other information protect the product in this container from excessive heat and direct sun

Inactive Ingredients

Inactive ingredients Water, Butyloctyl Salicylate, Propyheptyl Caprylate, Propanediol, Hydrogenated Coco nut Oil, Isodadecane, Caprylic/Capric Triglyceride, Glycerin, Dicaprylyl Carbonate, Polyglyceryl-6 Polyricinoleate, Sodium Chloride, Fusidium Coccineum Ferment Lysate Extract Filtrate, Nymphaea Alba Flower Extract, Protease, Nelum bo Nicifera Leaf Extract, Sacccharomyces Ferment, Crypto meria Japonica Leaf Extract, Methyl Methacrylate Crosspolymer, Disteardimonium Hectorite, Calcium Sodium Borosilicate, Triethoxycaprylylsilane, Polyglyceryl-2 Isostearate, 1,2-Hexanediol, Polyglyceryl-2 Dipolyhydroxystearate, Coco-Caprylate/Caprate, Caprylyl Glycol, Glyceryl Caprylate, Sorbitan Isostearate, Hectorite, Magnesium Sulfate, Butylene Glycol, Tocopherol

Questions

Question? : Call +82-80-023-1897 (International rates may apply)

Keep Out Of Children

* Keep out of Reach of Children. If swallowed, get medical help or contact a Poison Control Center right away.

Principal display panel